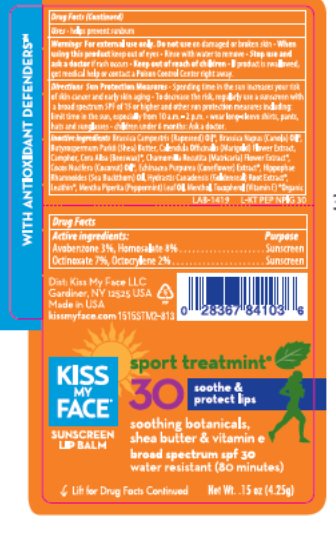 DRUG LABEL: Kiss My Face SPF 30 Sport Treatmint Lip Balm
NDC: 65364-222 | Form: STICK
Manufacturer: Kiss My Face
Category: otc | Type: HUMAN OTC DRUG LABEL
Date: 20150311

ACTIVE INGREDIENTS: OCTINOXATE 7.0 mg/1 g; OCTOCRYLENE 2 mg/1 g; AVOBENZONE 3.0 mg/1 g; HOMOSALATE 8.0 mg/1 g
INACTIVE INGREDIENTS: COCONUT OIL 17 mg/1 g; WHITE WAX 27 mg/1 g; .ALPHA.-TOCOPHEROL ACETATE 1.30 mg/1 g; SHEA BUTTER .1 mg/1 g; MENTHOL .3 mg/1 g; CANOLA OIL 28 mg/1 g

Drug Facts

Active ingredient

Avobenzone (3.0%), Homosalate (8.0%), Octinoxate (7.0%), Octocrylene (2.0%)

Purpose

Sunscreen

Keep Out of Reach of Children

If swallowed get medical help or contact a Poison Control Center right away.

Uses

Helps prevent sunburn.

Warnings

For external use only. Do not use on damaged or broken skin. When using this product keep out of eyes. Rinse with water to remove. Stop use and ask a doctor if rash occurs.

Directions

Apply liberally 15 minutes before sun exposure. Reapply: after 80 minutes of swimming or sweating, immediately after towel drying, at least every 2 hours. Sun Protection Measures: Spending time in the sun increases your risk of skin cancer and early skin aging. To decrease the risk, regularly use a sunscreen with a Broad Spectrum SPF of 15 or higher and other sun protection measures including: Limit time in the sun, especially from 10 AM – 2 PM . Wear long-sleeved shirts, pants, hats and sunglasses. Children under 6 months: Ask a doctor.

Inactive Ingredients

Canola Oil*, Beeswax*, Cocos Nucifera (Coconut) Oil*, Mentha Piperita (Peppermint)

Oil, Tocopherol, Lecithin*, Menthol, Camphor, Hippophae Rhamnoides Oil,

Butyrospermum Parkii (Shea Butter), Brassica Campestris (Rapeseed) Oil*, Hydrastis

Canadensis (Golden Seal) Root Extract*, Echinacea Purpurea Extract*, Calendula

Officinalis Flower Extract*, Chamomilla Recutita (Matricaria) Flower Extract*.

*